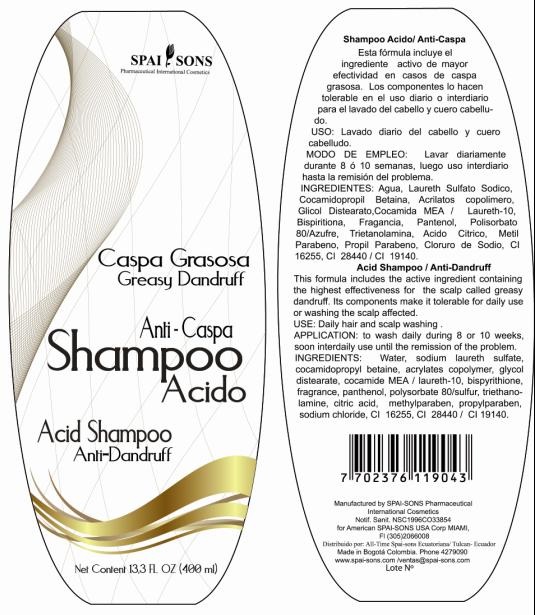 DRUG LABEL: SPAI-SONS
NDC: 66854-021 | Form: SHAMPOO
Manufacturer: SPAI-SONS PHARAMCUETICAL INTERNATIONAL COSMETICS
Category: otc | Type: HUMAN OTC DRUG LABEL
Date: 20120606

ACTIVE INGREDIENTS: SULFUR 0.4 mL/100 mL
INACTIVE INGREDIENTS: WATER; SODIUM LAURETH SULFATE; COCAMIDOPROPYL BETAINE; GLYCOL DISTEARATE; SODIUM LAURETH SULFATE; SODIUM LAURETH SULFATE; COCO MONOETHANOLAMIDE; LAURETH-10; DIPYRITHIONE; PANTHENOL; POLYSORBATE 80  ; TROLAMINE; CITRIC ACID MONOHYDRATE; METHYLPARABEN; PROPYLPARABEN; SODIUM CHLORIDE; FD&C RED NO. 40; FD&C YELLOW NO. 5

SPAI-SONS SHAMPOO ACIDO ANTI-CASPA / ACID SHAMPOO ANTI-DANDRUFF

ACTIVE INGREDIENT

This formula includes Biosulfur fluid, that is highest effectiveness for the scalp.

PURPOSE

This fromula includes the active ingredient containing the highest effectiveness for the scalp called greasy dandruff

KEEP OUT OF REACH OF CHILDREN

This product must be keep out reach of children

INDICATIONS AND USAGE

This product is for topical application. Wash the hair with the shampoo in the shower

WARNINGS

If this product is contact with eyes rinse immediately with water and consult your doctor.

DOSAGE AND ADMINISTRATION

To wash daily during 8 or 10 weeks, soon interdaily use until the remission of the problem. The product is for topical application.

INACTIVE INGREDIENT

Its components make it tolerable for daily use or washing the scalp affected

IMAGE OF THE LABEL